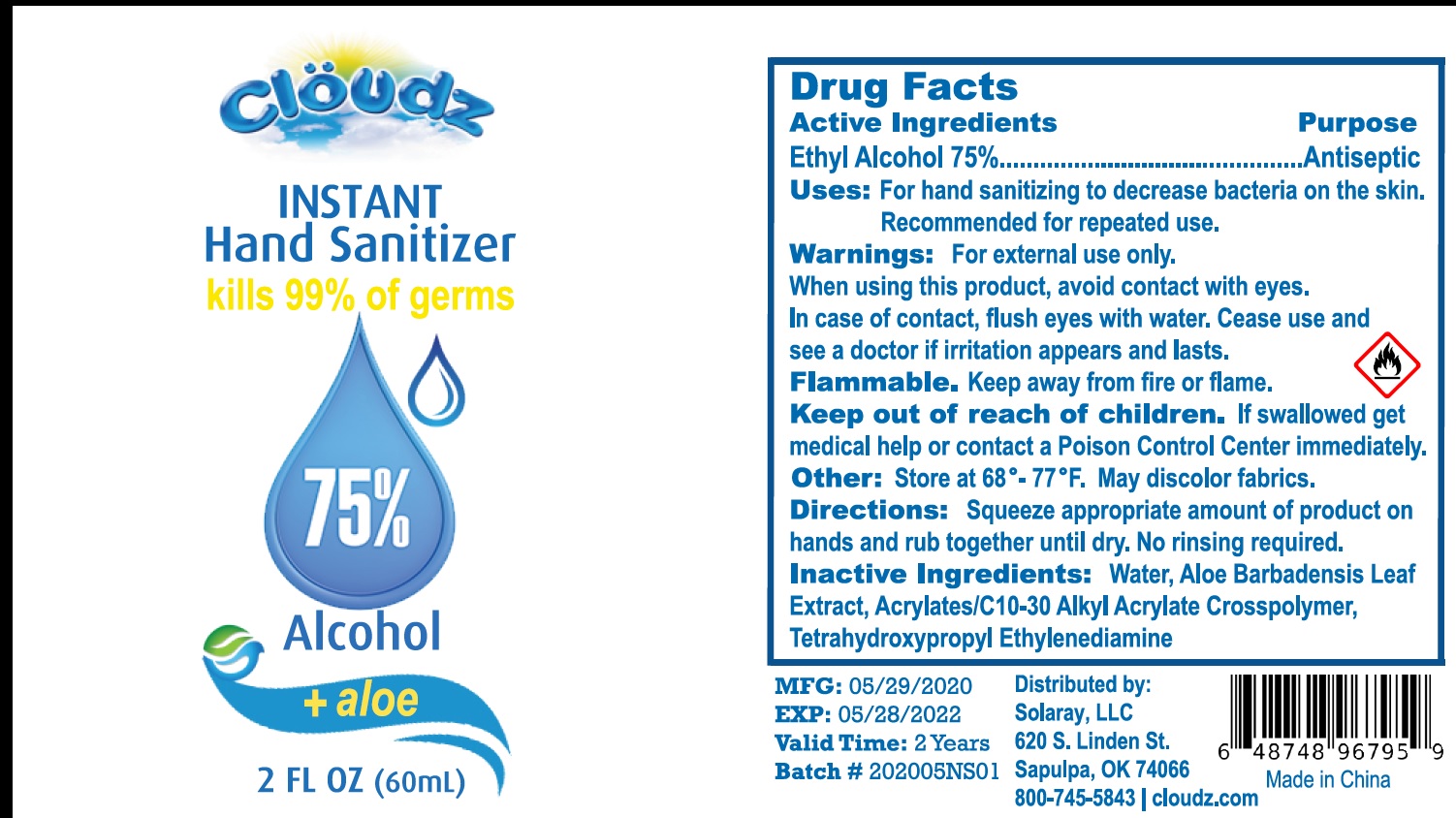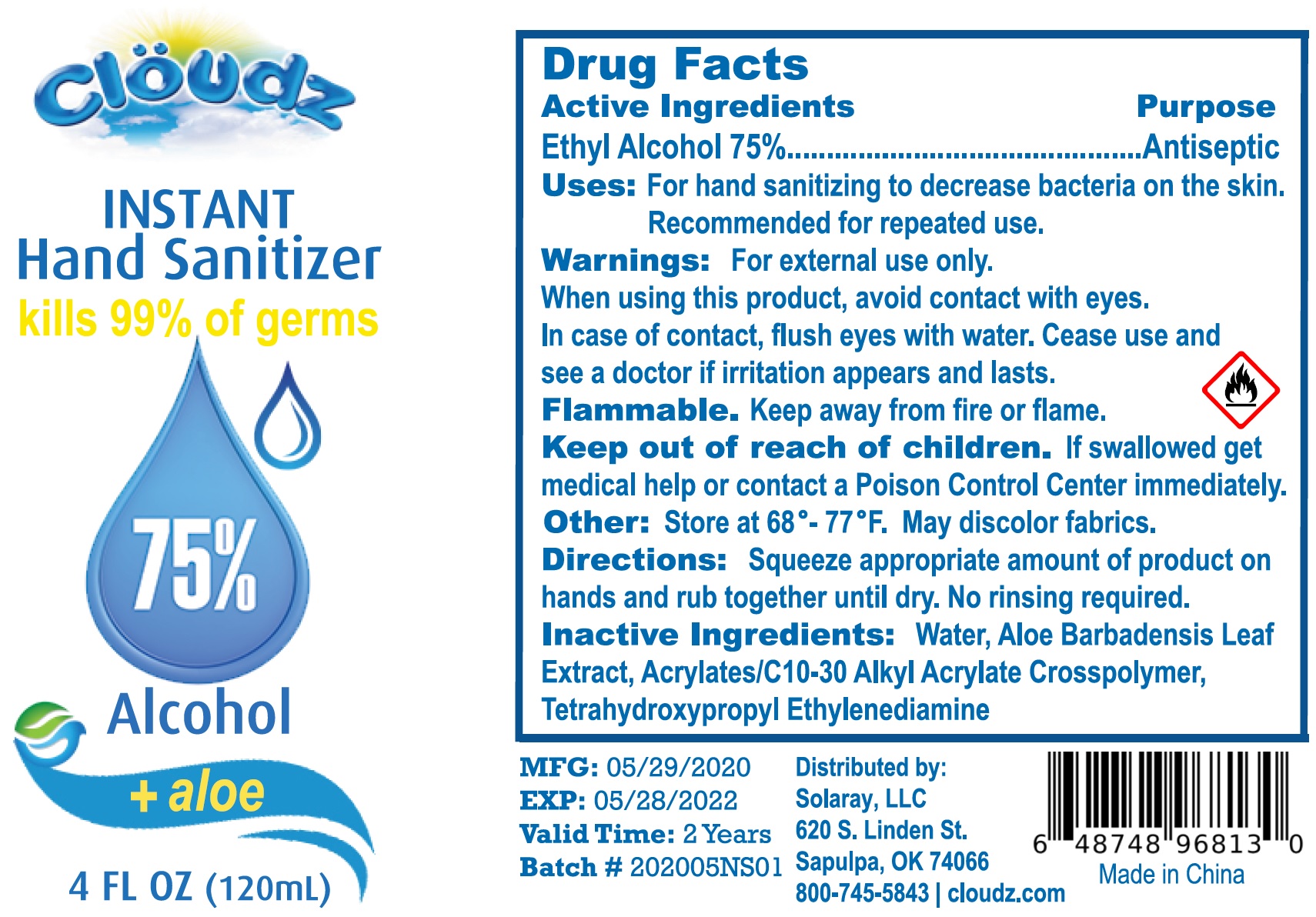 DRUG LABEL: Cloudz instant hand sanitizer
NDC: 79860-020 | Form: GEL
Manufacturer: Solaray LLC
Category: otc | Type: HUMAN OTC DRUG LABEL
Date: 20200806

ACTIVE INGREDIENTS: ALCOHOL 0.75 mL/1 mL
INACTIVE INGREDIENTS: WATER; ALOE VERA LEAF; EDETOL

Cloudz instant hand sanitizer

Active Ingredients

Ethyl Alcohol 75%

Purpose

Antiseptic

Uses:

For hand sanitizing to decrease bacteria on the skin. Recommended for repeated use.

Warnings:

For external use only.

When using this product,

avoid contact with eyes. In case of contact, flush eyes with water. Cease use and see a doctor if irritation appears and lasts.

Flammable. Keep away from fire or flame.

Keep out of reach of children.

If swallowed get medical help or contact a Poison Control Center immediately.

Other:

Store at 68°-77°F. May discolor fabrics.

Directioins:

Squeeze appropriate amount of product on hands and rub together until dry. No rinsing required.

Inactive Ingredients:

Water, Aloe Barbadensis Leaf Extract, Acrylates/C 10-30 Alkyl Acrylate Crosspolymer, Tetrahydroxypropyl Ethylenediamine